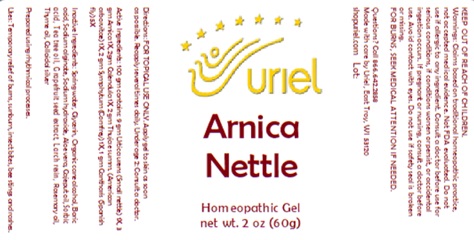 DRUG LABEL: Arnica Nettle
NDC: 48951-1401 | Form: GEL
Manufacturer: Uriel Pharmacy Inc.
Category: homeopathic | Type: HUMAN OTC DRUG LABEL
Date: 20250630

ACTIVE INGREDIENTS: CALENDULA OFFICINALIS FLOWERING TOP 1 [hp_X]/1 g; ARNICA MONTANA FLOWER 1 [hp_X]/1 g; THUJA OCCIDENTALIS WHOLE 1 [hp_X]/1 g; URTICA URENS 1 [hp_X]/1 g; COMFREY ROOT 1 [hp_X]/1 g; LYTTA VESICATORIA 5 [hp_X]/1 g
INACTIVE INGREDIENTS: SILVER; WATER; GLYCERIN; ALCOHOL; LARIX DECIDUA RESIN; BORIC ACID; SODIUM ALGINATE; ALOE VERA LEAF; CAJUPUT OIL; SODIUM HYDROXIDE; TEA TREE OIL; ROSEMARY OIL; SORBIC ACID; THYME OIL; CITRUS PARADISI SEED

Arnica Nettle

INDICATIONS AND USAGE

Directions: FOR TOPICAL USE ONLY.

DOSAGE AND ADMINISTRATION

Apply gel to skin as soon as possible. Reapply several times daily. Under age 2: Consult a doctor

ACTIVE INGREDIENT

Active Ingredients: 100 gm contains: 9 gm Urtica urens (Small nettle) 1X, 3 gm Arnica 1X, 2gm Calendula 1X, 2 gm Thuja e summ. (American arborvitae) 1X, 2 gm Symphytum (Comfrey) 1X, 1 gm Cantharis (Spanish fly) 5X

INACTIVE INGREDIENT

Inactive Ingredients: Spring water, Glycerin, Organic cane alcohol, Boric acid, Sodium alginate, Sodium hydroxide, Aloe vera, Cajeput oil, Sorbic acid, Tea tree oil, Grapefruit seed extract, Larch resin, Rosemary oil, Thyme oil, Colloidal silver

Prepared using rhythmical processes.

PURPOSE

Uses: Temporary relief of burns, sunburn, insect bites, bee stings and rashes.

KEEP OUT OF REACH OF CHILDREN.

WARNINGS

Warnings: Claims based on traditional homeopathic practice, not accepted medical evidence. Not FDA evaluated. Do not use if allergic to any ingredient. Consult a doctor before use for serious conditions, if conditions worsen or persist, or accidental ingestion occurs. If pregnant or nursing, consult a doctor before use. Avoid contact with eyes. Do not use if safety seal is broken or missing.

FOR BURNS, SEEK MEDICAL ATTENTION IF NEEDED.

Questions? Call 866.642.2858
Made with care by Uriel, East Troy, WI 53120
shopuriel.com Lot: